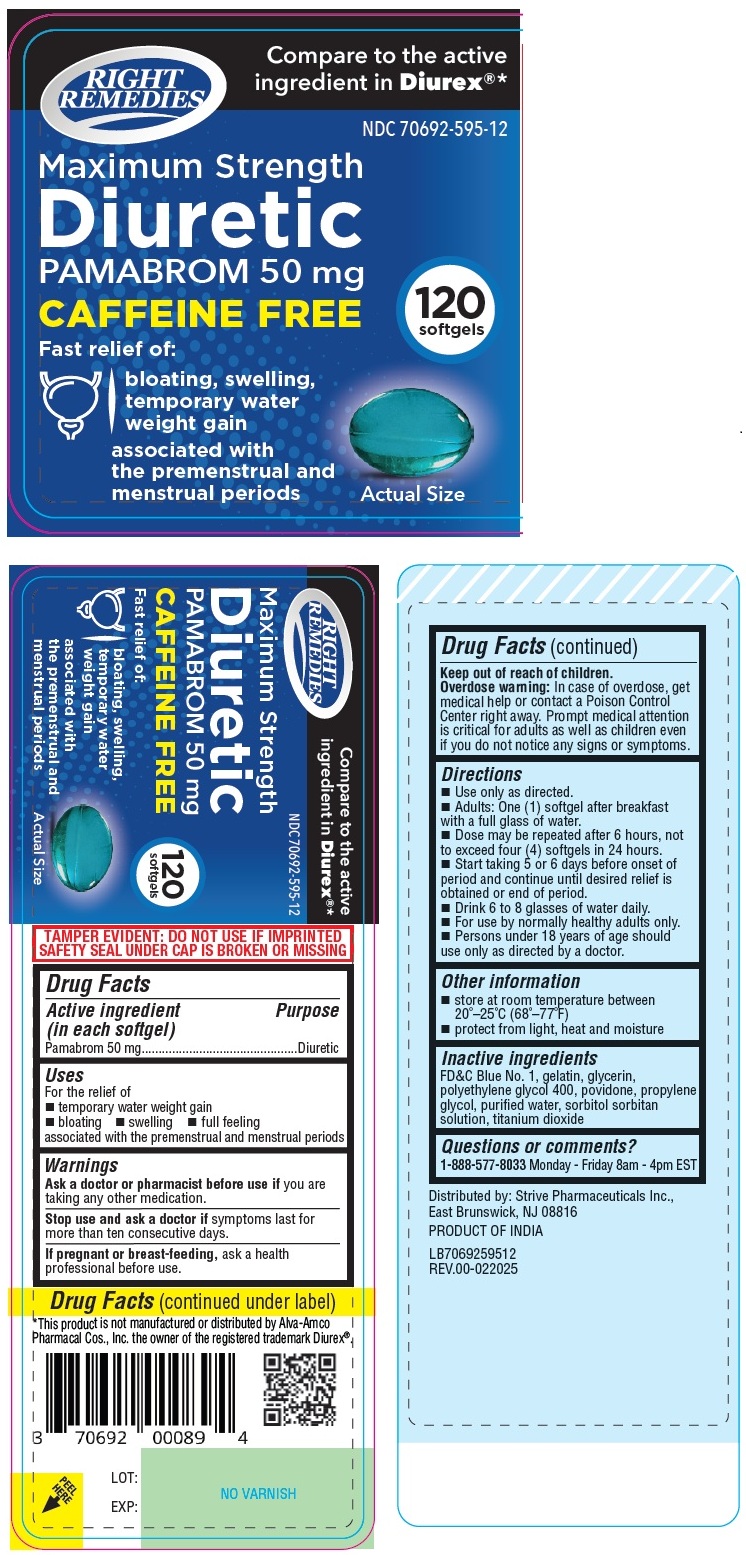 DRUG LABEL: RIGHT REMEDIES Maximum Strength Diuretic
NDC: 70692-595 | Form: CAPSULE, LIQUID FILLED
Manufacturer: Strive Pharmaceuticals Inc.
Category: otc | Type: HUMAN OTC DRUG LABEL
Date: 20250507

ACTIVE INGREDIENTS: PAMABROM 50 mg/1 1
INACTIVE INGREDIENTS: FD&C BLUE NO. 1; GELATIN, UNSPECIFIED; GLYCERIN; POLYETHYLENE GLYCOL 400; POVIDONE, UNSPECIFIED; PROPYLENE GLYCOL; WATER; SORBITOL; SORBITAN; TITANIUM DIOXIDE

RIGHT REMEDIES Maximum Strength Diuretic softgels

Active ingredient (in each softgel)

Pamabrom 50 mg

Purpose

Diuretic

Uses

For the relief of
• temporary water weight gain
• bloating • swelling • full feeling associated with the premenstrual and menstrual periods

Warnings

Ask a doctor or pharmacist before use if you are taking any other medication.

Stop use and ask a doctor if symptoms last for more than ten consecutive days.

If pregnant or breast-feeding, ask a health professional before use.

Keep out of reach of children.
Overdose warning: In case of overdose, get medical help or contact a Poison Control Center right away. Prompt medical attention is critical for adults as well as children even if you do not notice any signs or symptoms.

Directions

• Use only as directed.
• Adults: One (1) softgel after breakfast with a full glass of water.
• Dose may be repeated after 6 hours, not to exceed four (4) softgels in 24 hours.
• Start taking 5 or 6 days before onset of period and continue until desired relief is obtained or end of period.
• Drink 6 to 8 glasses of water daily.
• For use by normally healthy adults only.
• Persons under 18 years of age should use only as directed by a doctor.

Other information

• store at room temperature between 20°–25°C (68°–77°F)
• protect from light, heat and moisture

Inactive ingredients

FD&C Blue No. 1, gelatin, glycerin, polyethylene glycol 400, povidone, propylene glycol, purified water, sorbitol sorbitan solution, titanium dioxide

Questions or comments?

1-888-577-8033 Monday - Friday 8am - 4pm EST

Compare to the active ingredient in Diurex®*

CAFFEINE FREE

Fast relief of:
bloating, swelling, temporary water weight gain associated with the premenstrual and menstrual periods

TAMPER EVIDENT: DO NOT USE IF IMPRINTED SAFETY SEAL UNDER CAP IS BROKEN OR MISSING

*This product is not manufactured or distributed by Alva-Amco Pharmacal Cos., Inc. the owner of the registered trademark Diurex®.

Distributed by: Strive Pharmaceuticals Inc.,
East Brunswick, NJ 08816

PRODUCT OF INDIA